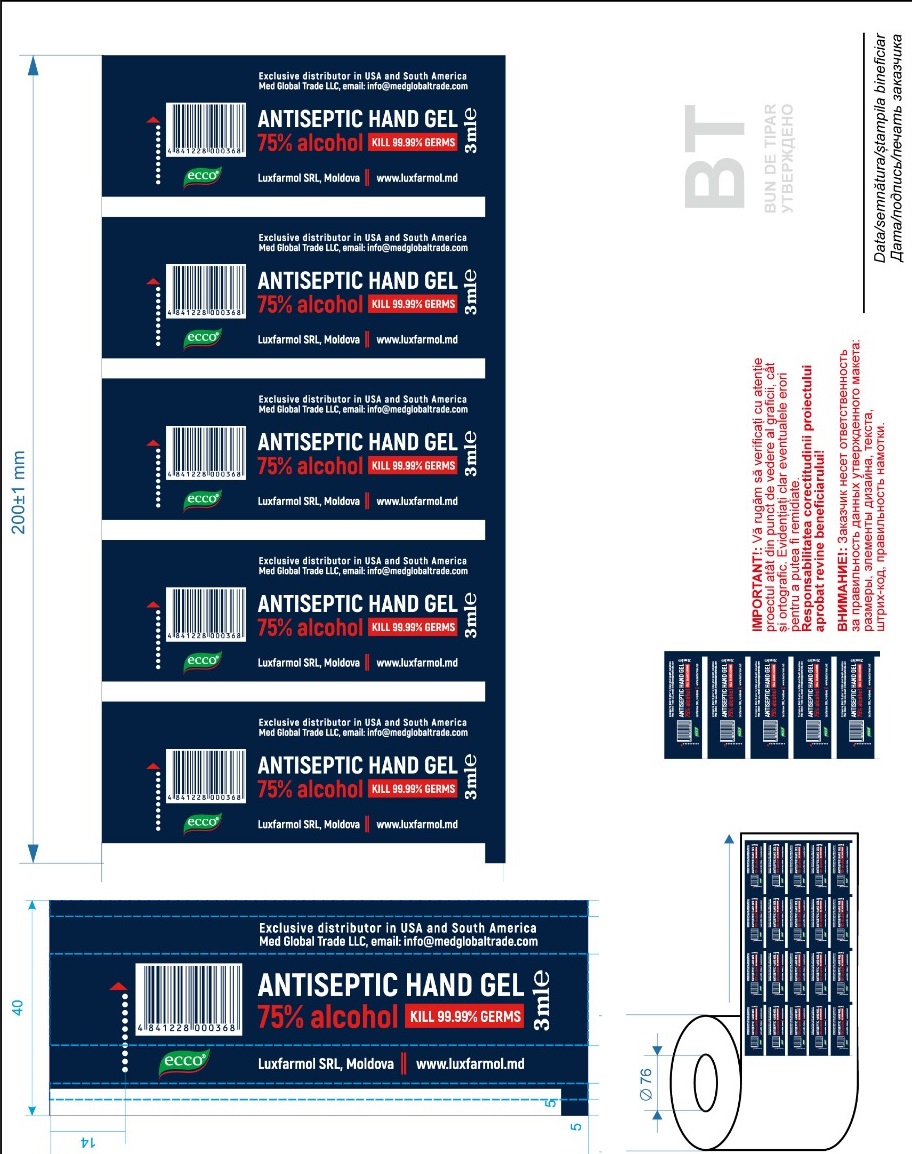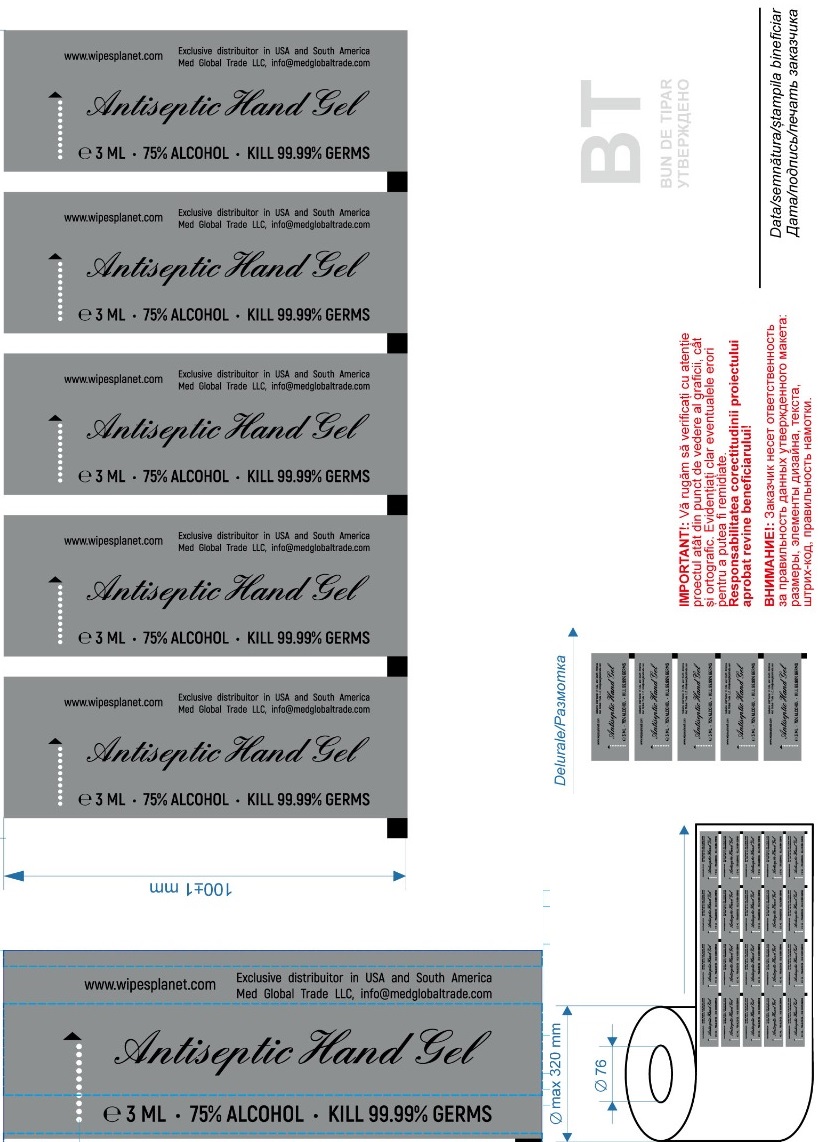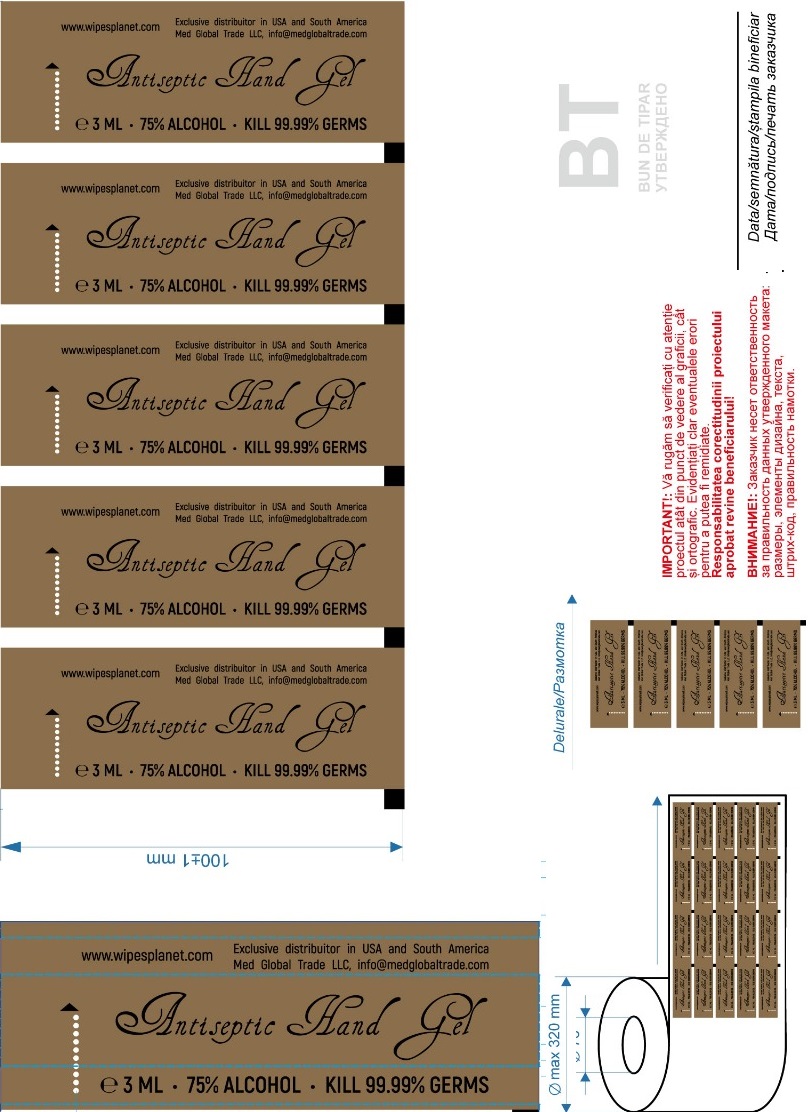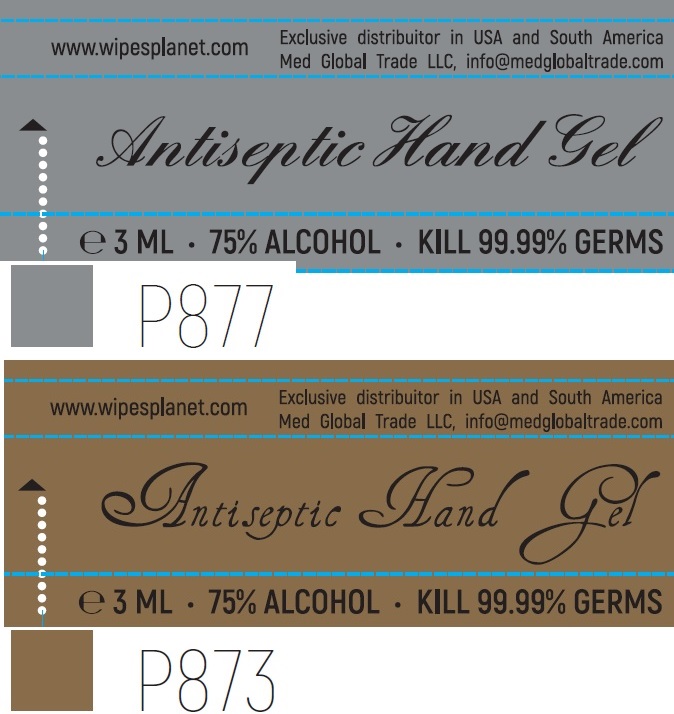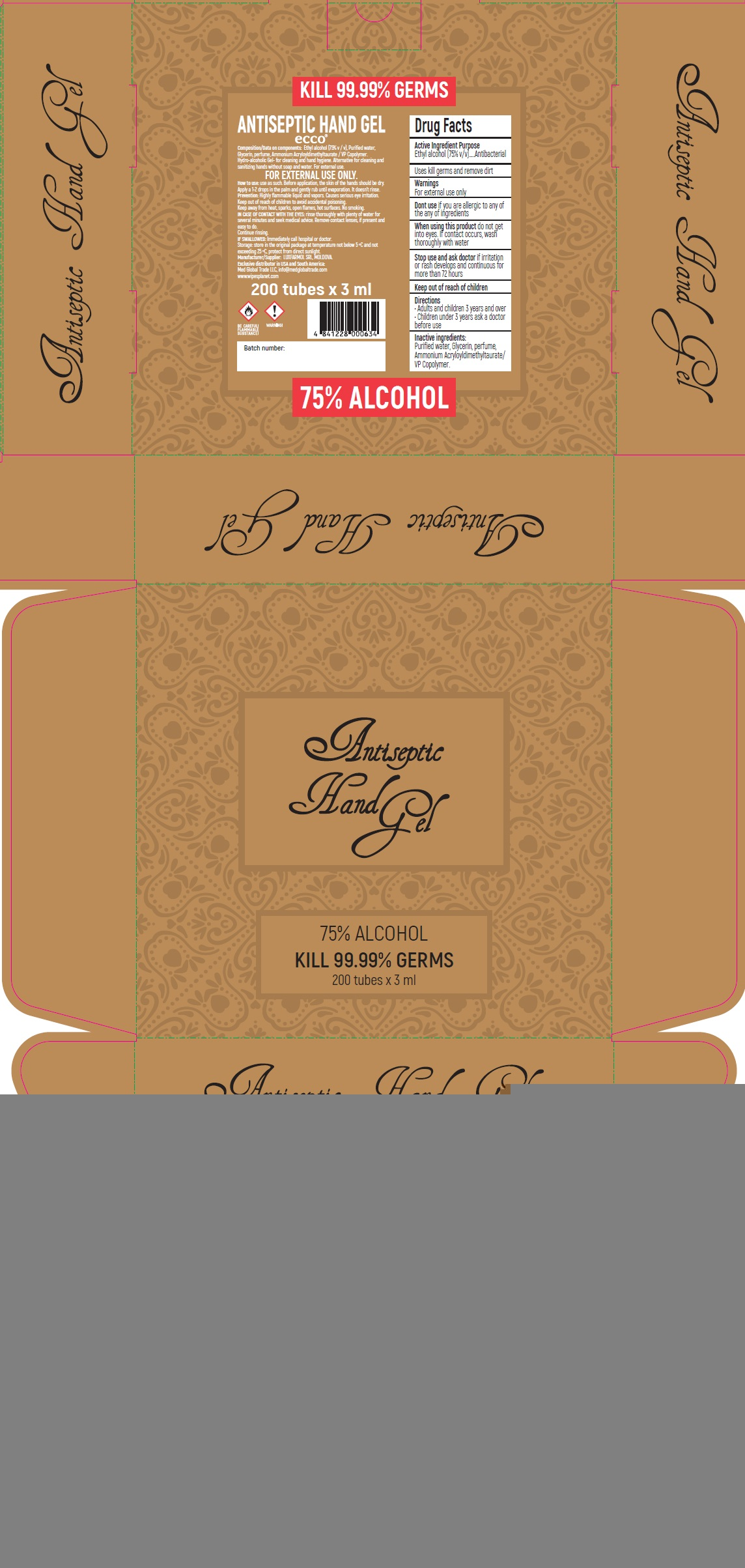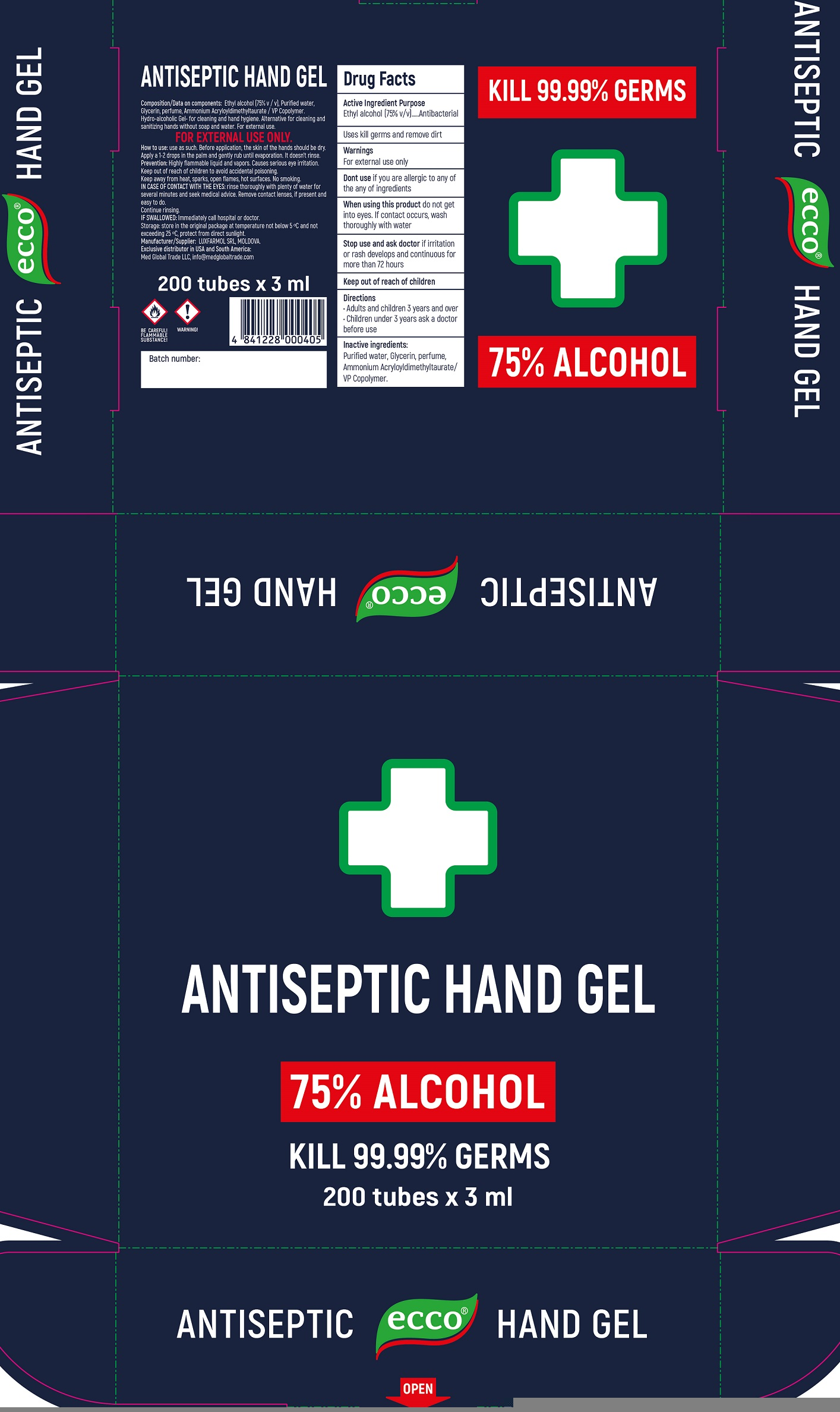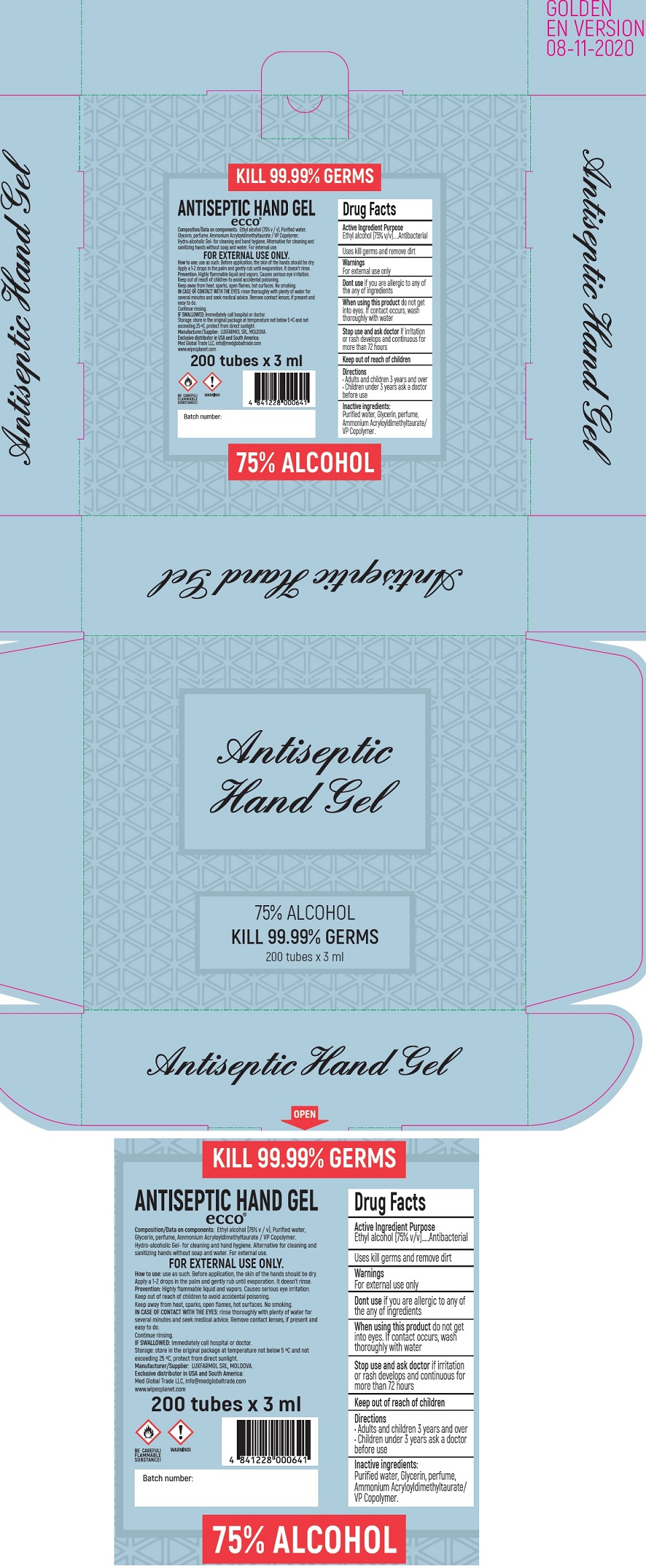 DRUG LABEL: ECCO Antiseptic Hand Gel
NDC: 79164-000 | Form: GEL
Manufacturer: LUXFARMOL, SOCIETATEA CU RASPUNDERE LIMITATA
Category: otc | Type: HUMAN OTC DRUG LABEL
Date: 20210202

ACTIVE INGREDIENTS: ALCOHOL 75 mL/100 mL
INACTIVE INGREDIENTS: WATER; GLYCERIN; AMMONIUM ACRYLOYLDIMETHYLTAURATE/VP COPOLYMER

ECCO Antiseptic Hand Gel, 75% Alcohol

Active Ingredient

Ethyl alcohol (75% v/v)

Purpose

Antibacterial

Uses

kill germs and remove dirt

Warnings

For external use only

Dont use

if you are allergic to any of the any of ingredients

When using this product

do not get into eyes. If contact occurs, wash thoroughly with water

Stop use and ask doctor

if irritation or rash develops and continuous for more than 72 hours

Directions

• Adults and children 3 years and over
• Children under 3 years ask a doctor before use

Inactive ingredients:

Purified water, Glycerin, perfume, Ammonium Acryloyldimethyltaurate/ VP Copolymer.